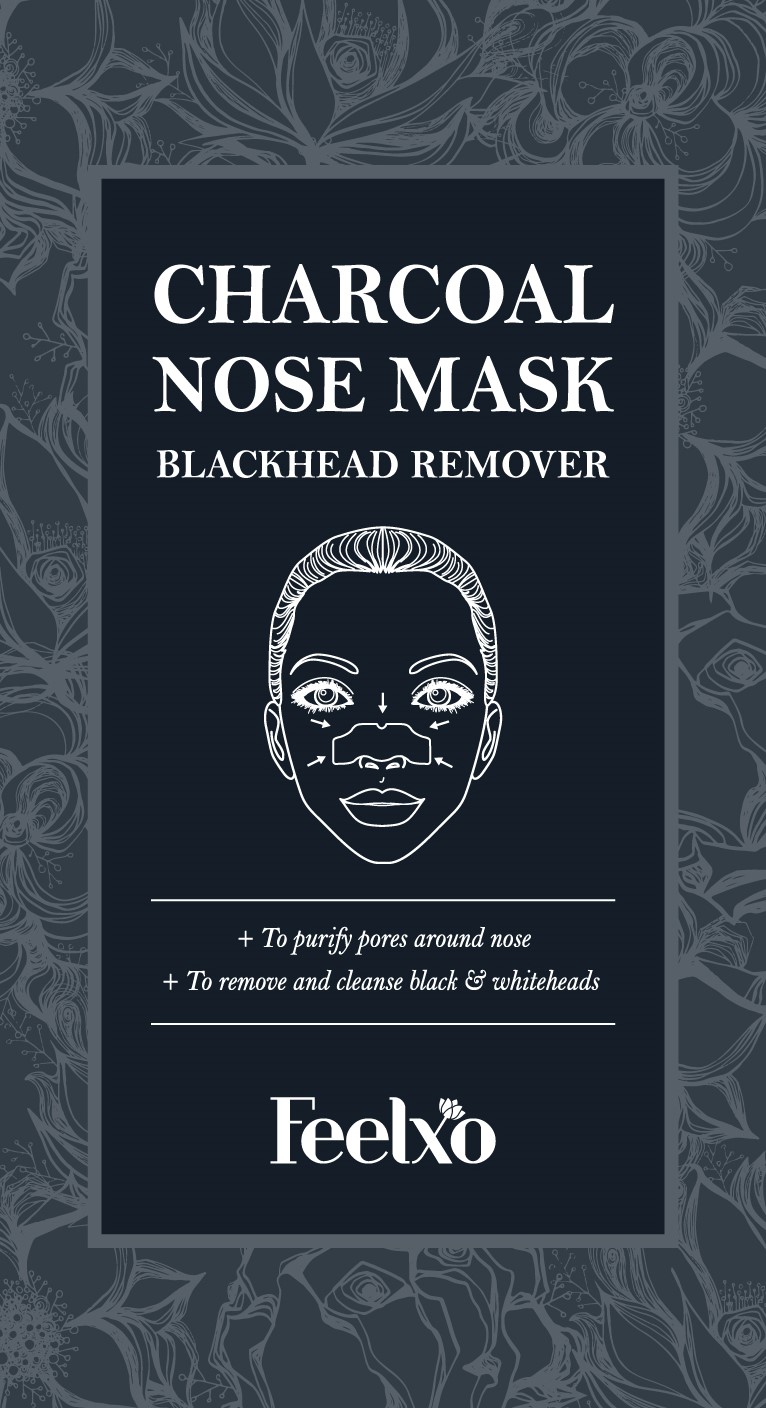 DRUG LABEL: Charcoal Nose Mask Blackhead Remover
NDC: 71694-0005 | Form: LIQUID
Manufacturer: Feelxo
Category: otc | Type: HUMAN OTC DRUG LABEL
Date: 20181114

ACTIVE INGREDIENTS: WITCH HAZEL 0.01 g/100 g
INACTIVE INGREDIENTS: WATER; ACTIVATED CHARCOAL

Drug Facts

ACTIVE INGREDIENT

Witch Hazel

INACTIVE INGREDIENT

Allantoin, Charcoal powder, Aloe Barbadensis Leaf Extract, etc.

PURPOSE

Skin Protectant

keep out of reach of the children

INDICATIONS AND USAGE

1. Wash your face and make sure it is free of any creams of lotions.
2. Thoroughly wet your nose with water.
3. Remove the protective film with dry hands, then attach the nose mask on your nose and wait for 10~15 minutes.
4. When the mask is completely dry, remove the mask slowly from the edge.

WARNINGS

- Keep the mask in the fridge before use to enjoy more cooling & soothing effect
- Feelxo sheet mask can be used for all skin types, however it is not recommended for those who need medical skin care.

DOSAGE AND ADMINISTRATION

for external use only